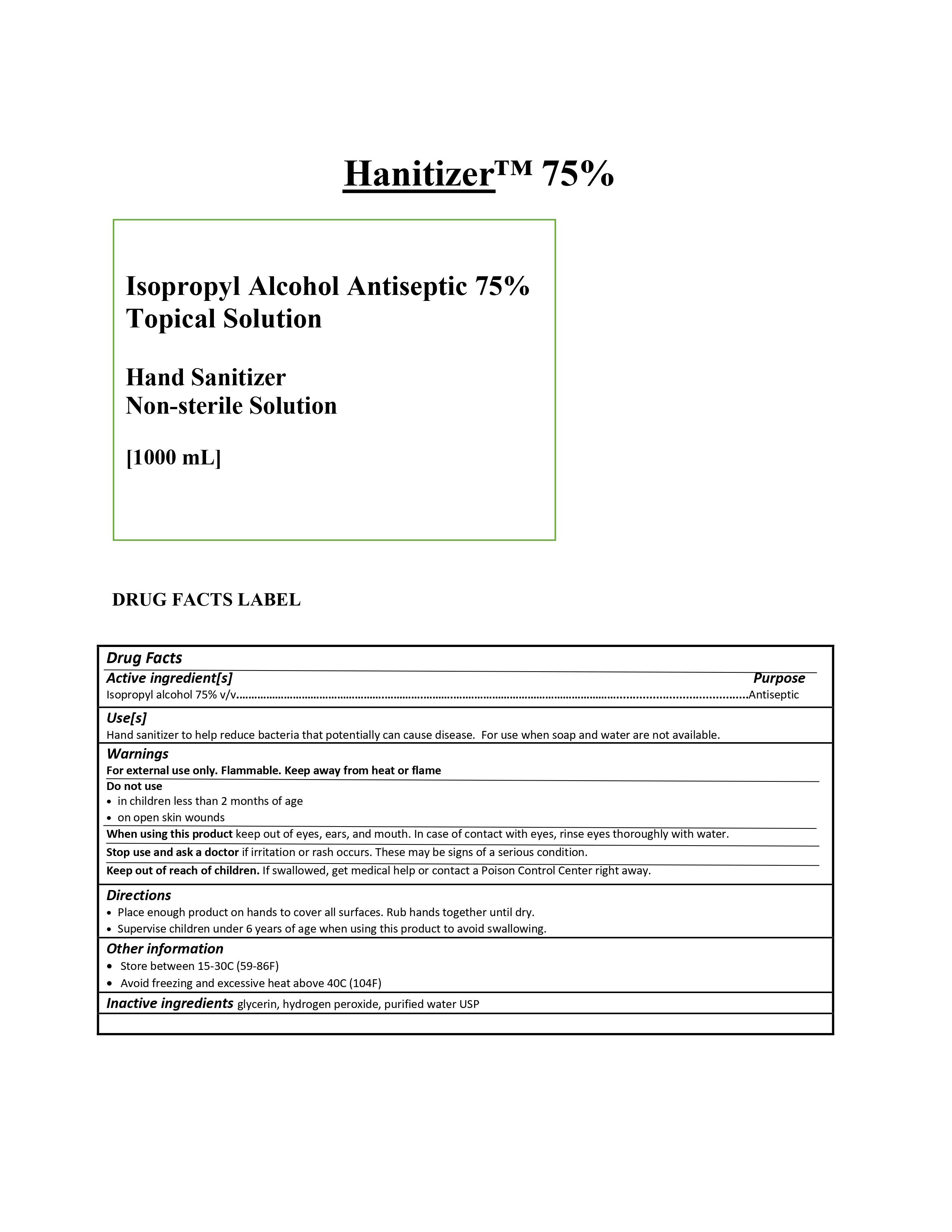 DRUG LABEL: Hanitizer
NDC: 74132-900 | Form: LIQUID
Manufacturer: Amtrust Biochemical Corp.
Category: otc | Type: HUMAN OTC DRUG LABEL
Date: 20200325

ACTIVE INGREDIENTS: ISOPROPYL ALCOHOL 0.75 L/1 L
INACTIVE INGREDIENTS: WATER 0.23425 L/1 L; HYDROGEN PEROXIDE 0.00125 L/1 L; GLYCERIN 0.0145 L/1 L

ACTIVE INGREDIENT

Isopropyl Alcohol 75% v/v

PURPOSE

Antiseptic

INDICATIONS AND USAGE

Hand sanitizer to help reduce bacteria that potentially can cause disease. For use when soap and water are not available.

WARNINGS

For external use only. Flammable. Keep away from heat or flame.

Do not use in children less than 2 months of age or on open wounds

Keep out of reach of children. If swallowed, get medical help or contact a Poison Control Center right away.

Directions
• Place enough product on hands to cover all surfaces. Rub hands together until dry.
• Supervise children under 6 years of age when using this product to avoid swallowing.

Other information
• Store between 15-30C (59-86F)
• Avoid freezing and excessive heat above 40C (104F)

INACTIVE INGREDIENT

glycerin, hydrogen peroxide, purified water

When using this product keep out of eyes, ears, and mouth. In case of contact with eyes, rinse eyes
thoroughly with water.

Stop use and ask a doctor if irritation or rash occurs. These may be signs of a serious condition.